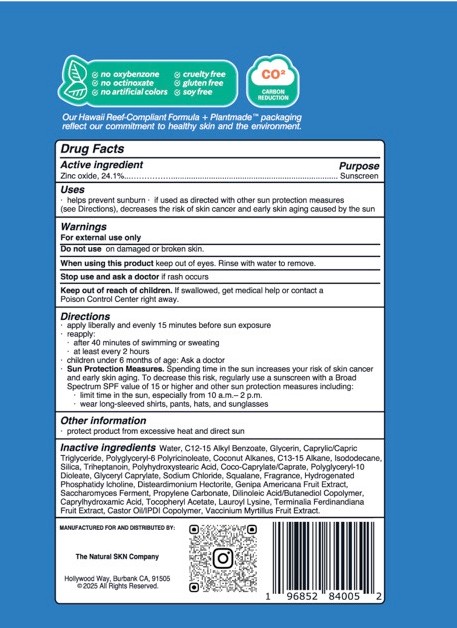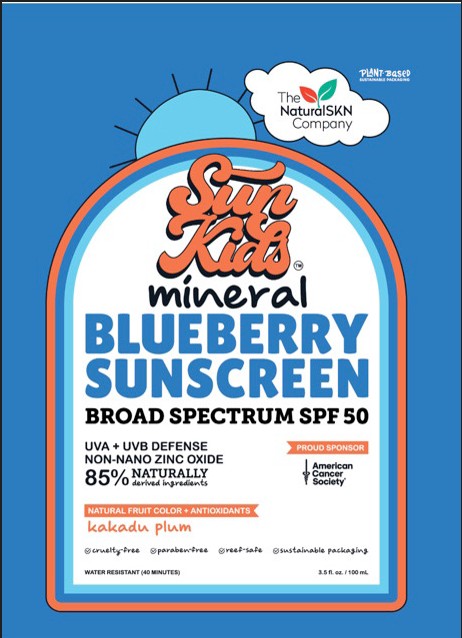 DRUG LABEL: Sun Kids mineral BLUEBERRY SUNSCREEN BROAD SPECTRUM SPF 50
NDC: 87138-002 | Form: CREAM
Manufacturer: The Natural SKN Company
Category: otc | Type: HUMAN OTC DRUG LABEL
Date: 20251007

ACTIVE INGREDIENTS: ZINC OXIDE 241 mg/1 mL
INACTIVE INGREDIENTS: COCO-CAPRYLATE/CAPRATE; TRIHEPTANOIN; SODIUM CHLORIDE; C13-15 ALKANE; GLYCERIN; ISODODECANE; SQUALANE; POLYGLYCERYL-6 POLYRICINOLEATE; POLYGLYCERYL-10 DIOLEATE; CAPRYLHYDROXAMIC ACID; DILINOLEIC ACID/BUTANEDIOL COPOLYMER; CASTOR OIL/IPDI COPOLYMER; GLYCERYL CAPRYLATE; POLYHYDROXYSTEARIC ACID (2300 MW); PROPYLENE CARBONATE; WATER; C12-15 ALKYL BENZOATE; COCONUT ALKANES; CAPRYLIC/CAPRIC TRIGLYCERIDE; SILICA; DISTEARDIMONIUM HECTORITE; LAUROYL LYSINE

ACTIVE INGREDIENT

Zinc Oxide 24.1%

Warnings
For external use only
Do not use on damaged or broken skin.
When using this product keep out of eyes. Rinse with water to remove.
Stop use and ask a doctor if rash occurs
Keep out of reach of children. If swallowed, get medical help or contact a
Poison Control Center right away.

Uses

. helps prevent sunburn . if used as directed with other sun protection measures
(see Directions), decreases the risk of skin cancer and early skin aging caused by the sun

Do not use on damaged or broken skin.

Directions

. apply liberally and evenly 15 minutes before sun exposure
reapply:
. after 40 minutes of swimming or sweating
. at least every 2 hours
. children under 6 months of age: Ask a doctor
. Sun Protection Measures. Spending time in the sun increases your risk of skin cancer
and early skin aging. To decrease this risk, regularly use a sunscreen with a Broad
Spectrum SPF value of 15 or higher and other sun protection measures including:
. limit time in the sun, especially from 10 a.m .- 2 p.m.
· wear long-sleeved shirts, pants, hats, and sunglasses

INACTIVE INGREDIENT

Other Ingredients:
Water (Aqua)
C12-15 Alkyl Benzoate
Caprylic/Capric Triglyceride
C13-15 Alkane
Glycerin
Polyglyceryl-6 Polyricinoleate
Coconut Alkanes
Silica
Isododecane
Triheptanoin
Sodium Chloride
Squalane (Olive derived)
Fragrance
Terminalia Ferdinandiana Fruit Extract
Vaccinium Myrtillus (Blueberry) Fruit Extract
Coco-Caprylate/Caprate
Polyglyceryl-10 Dioleate
Disteardimonium Hectorite
Hydrogenated Phosphatidylcholine
Tocopheryl Acetate (Vitamin E)
Caprylhydroxamic Acid
Dilinoleic Acid/Butanediol Copolymer
Castor Oil/IPDI Copolymer
Glyceryl Caprylate
Polyhydroxystearic Acid
Genipa Aericana Fruit Extract
Propylene Carbonate
Saccharomyces Ferment
Lauroyl Lysine

STORAGE AND HANDLING

. protect product from excessive heat and direct sun

Keep out of reach of children. If swallowed, get medical help or contact a Poison Control Center right away